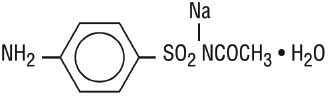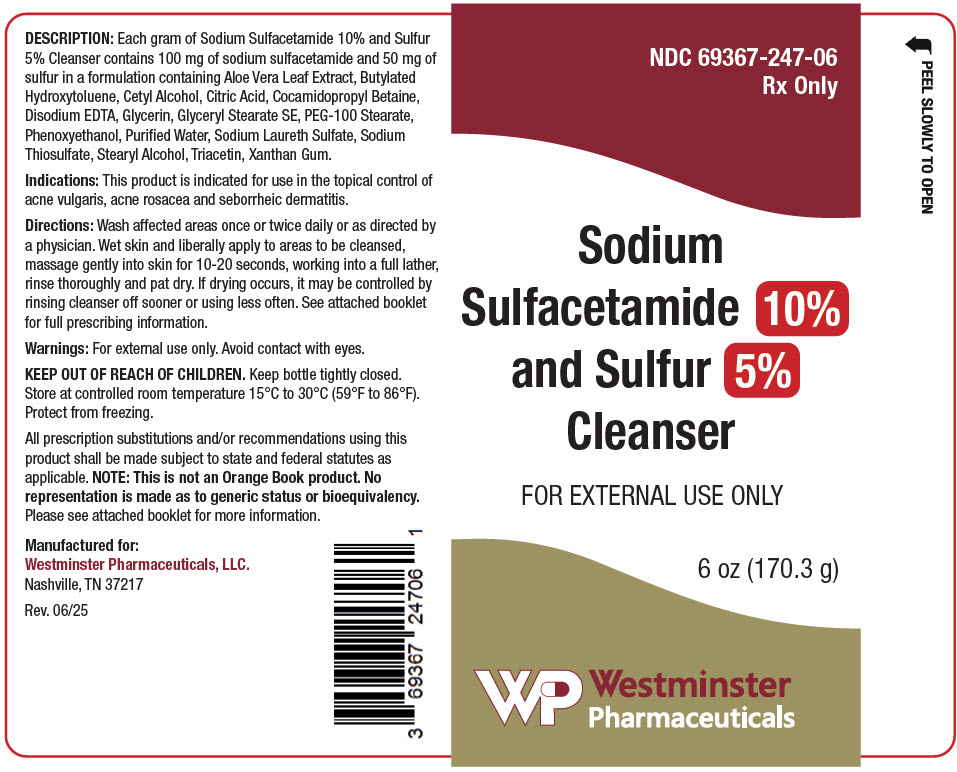 DRUG LABEL: SODIUM SULFACETAMIDE, SULFUR
NDC: 69367-247 | Form: LIQUID
Manufacturer: Westminster Pharmaceuticals, LLC
Category: prescription | Type: HUMAN PRESCRIPTION DRUG LABEL
Date: 20250701

ACTIVE INGREDIENTS: SULFACETAMIDE SODIUM 100 mg/1 g; SULFUR 50 mg/1 g
INACTIVE INGREDIENTS: BUTYLATED HYDROXYTOLUENE; CETYL ALCOHOL; COCAMIDOPROPYL BETAINE; EDETATE DISODIUM ANHYDROUS; GLYCERIN; GLYCERYL STEARATE SE; PEG-100 STEARATE; WATER; SODIUM THIOSULFATE; STEARYL ALCOHOL; TRIACETIN; ALOE; CITRIC ACID MONOHYDRATE; PHENOXYETHANOL; SODIUM LAURETH-3 SULFATE; XANTHAN GUM

Sodium Sulfacetamide 10% and Sulfur 5% Cleanser

Rx Only

FOR EXTERNAL USE ONLY. NOT FOR OPHTHALMIC USE.

DESCRIPTION

Each gram of Sodium Sulfacetamide 10% and Sulfur 5% Cleanser contains 100 mg of sodium sulfacetamide and 50 mg of sulfur in a formulation containing Aloe Vera Leaf Extract, Butylated Hydroxytoluene, Cetyl Alcohol, Citric Acid, Cocamidopropyl Betaine, Disodium EDTA, Glycerin, Glyceryl Stearate SE, PEG-100 Stearate, Phenoxyethanol, Purified Water, Sodium Laureth Sulfate, Sodium Thiosulfate, Stearyl Alcohol, Triacetin, Xanthan Gum.

Sodium sulfacetamide is a sulfonamide with antibacterial activity while sulfur acts as a keratolytic agent. Chemically sodium sulfacetamide is N-[(4-aminophenyl) sulfonyl]-acetamide, monosodium salt, monohydrate. The structural formula is:

CLINICAL PHARMACOLOGY

The most widely accepted mechanism of action of sulfonamides is the Woods-Fildes theory, which is based on the fact that sulfonamides act as competitive antagonists to para-aminobenzoic acid (PABA), an essential component for bacterial growth. While absorption through intact skin has not been determined, sodium sulfacetamide is readily absorbed from the gastrointestinal tract when taken orally and excreted in the urine, largely unchanged. The biological half-life has variously been reported as 7 to 12.8 hours. The exact mode of action of sulfur in the treatment of acne is known, but it has been reported that it inhibits the growth of Propionibacterium acnes and the formation of free fatty acids.

INDICATIONS

Sodium Sulfacetamide 10% and Sulfur 5% Cleanser is indicated in the topical control of acne vulgaris, acne rosacea and seborrheic dermatitis.

CONTRAINDICATIONS

Sodium Sulfacetamide 10% and Sulfur 5% Cleanser is contraindicated for use by patients having known hypersensitivity to sulfonamides, sulfur or any other component of this preparation. Sodium Sulfacetamide 10% and Sulfur 5% Cleanser is not to be used by patients with kidney disease.

WARNINGS

Although rare, sensitivity to sodium sulfacetamide may occur. Therefore, caution and careful supervision should be observed when prescribing this drug for patients who may be prone to hypersensitivity to topical sulfonamides. Systemic toxic reactions such as agranulocytosis, acute hemolytic anemia, purpura hemorrhagica, drug fever, jaundice, and contact dermatitis indicate hypersensitivity to sulfonamides. Particular caution should be employed if areas of denuded or abraded skin are involved.

FOR EXTERNAL USE ONLY. Keep away from eyes. keep out of reach of children. In case of accidental ingestion contact a poison control center immediately. Keep container tightly closed.

PRECAUTIONS

General

If irritation develops, use of the product should be discontinued and appropriate therapy instituted. Patients should be carefully observed for possible local irritation or sensitization during long-term therapy. The object of this therapy is to achieve desquamation without irritation, but sodium sulfacetamide and sulfur can cause reddening and scaling of the epidermis. These side effects are not unusual in the treatment of acne vulgaris, but patients should be cautioned about the possibility.

Information for Patients

Avoid contact with eyes, eyelids, lips and mucous membranes. If accidental contact occurs, rinse with water. If excessive irritation develops, discontinue use and consult your physician.

Carcinogenesis, Mutagenesis and Impairment of Fertility

Long-term studies in animals have not been performed to evaluate carcinogenic potential.

Pregnancy

Category C

Animal reproduction studies have not been conducted with Sodium Sulfacetamide 10% and Sulfur 5% Cleanser. It is also not known whether Sodium Sulfacetamide 10% and Sulfur 5% Cleanser can cause fetal harm when administered to a pregnant woman or can affect reproduction capacity. Sodium Sulfacetamide 10% and Sulfur 5% Cleanser should be given to a pregnant woman only if clearly needed.

Nursing Mothers

It is not known whether sodium sulfacetamide is excreted in the human milk following topical use of Sodium Sulfacetamide 10% and Sulfur 5% Cleanser. However, small amounts of orally administered sulfonamides have been reported to be eliminated in human milk. In view of this and because many drugs are excreted in human milk, caution should be exercised when Sodium Sulfacetamide 10% and Sulfur 5% Cleanser is administered to a nursing woman.

Pediatric Use

Safety and effectiveness in children under the age of 12 have not been established.

ADVERSE REACTIONS

Although rare, sodium sulfacetamide may cause local irritation.

Call your doctor for medical advice about side effects. To report a serious adverse event, please contact Westminster Pharmaceuticals at 1-844-221-7294

DOSAGE AND ADMINISTRATION

Apply Sodium Sulfacetamide 10% and Sulfur 5% Cleanser once or twice daily to affected areas, or as directed by your physician. Wet skin and liberally apply to areas to be cleansed. Massage gently into skin for 10-20 seconds, working into a full lather, rinse thoroughly and pat dry. If drying occurs, it may be controlled by rinsing off Sodium Sulfacetamide 10% and Sulfur 5% Cleanser sooner or using less often.

HOW SUPPLIED

Sodium Sulfacetamide 10% and Sulfur 5% Cleanser is available in 6 oz. (170.3 g) bottles, NDC 69367-247-06, 8 oz. (227 g), NDC 69367-247-08, and 12 oz. (340.2 g) bottles, NDC 69367-247-12.

STORAGE AND HANDLING

Store at 15°C to 30°C (59°F to 86°F). Protect from freezing.

KEEP THIS AND ALL MEDICATIONS OUT OF THE REACH OF CHILDREN

All prescription substitutions and/or recommendations using this product shall be made subject to state and federal statutes as applicable. NOTE: This is not an Orange Book product. No representation is made as to generic status or bioequivalency. Each person recommending a prescription substitution using this product shall make such recommendations based on each such person's professional opinion and knowledge, upon evaluating the active ingredients, excipients, inactive ingredients and chemical formulation information provided herein.

Manufactured for:
Westminster Pharmaceuticals, LLC
Nashville, TN 37217

Rev. 06/25

PRINCIPAL DISPLAY PANEL - 170.3 g Bottle Label

NDC 69367-247-06
Rx Only

Sodium
Sulfacetamide 10%
and Sulfur 5%
Cleanser

FOR EXTERNAL USE ONLY

6 oz (170.3 g)

Westminster
Pharmaceuticals